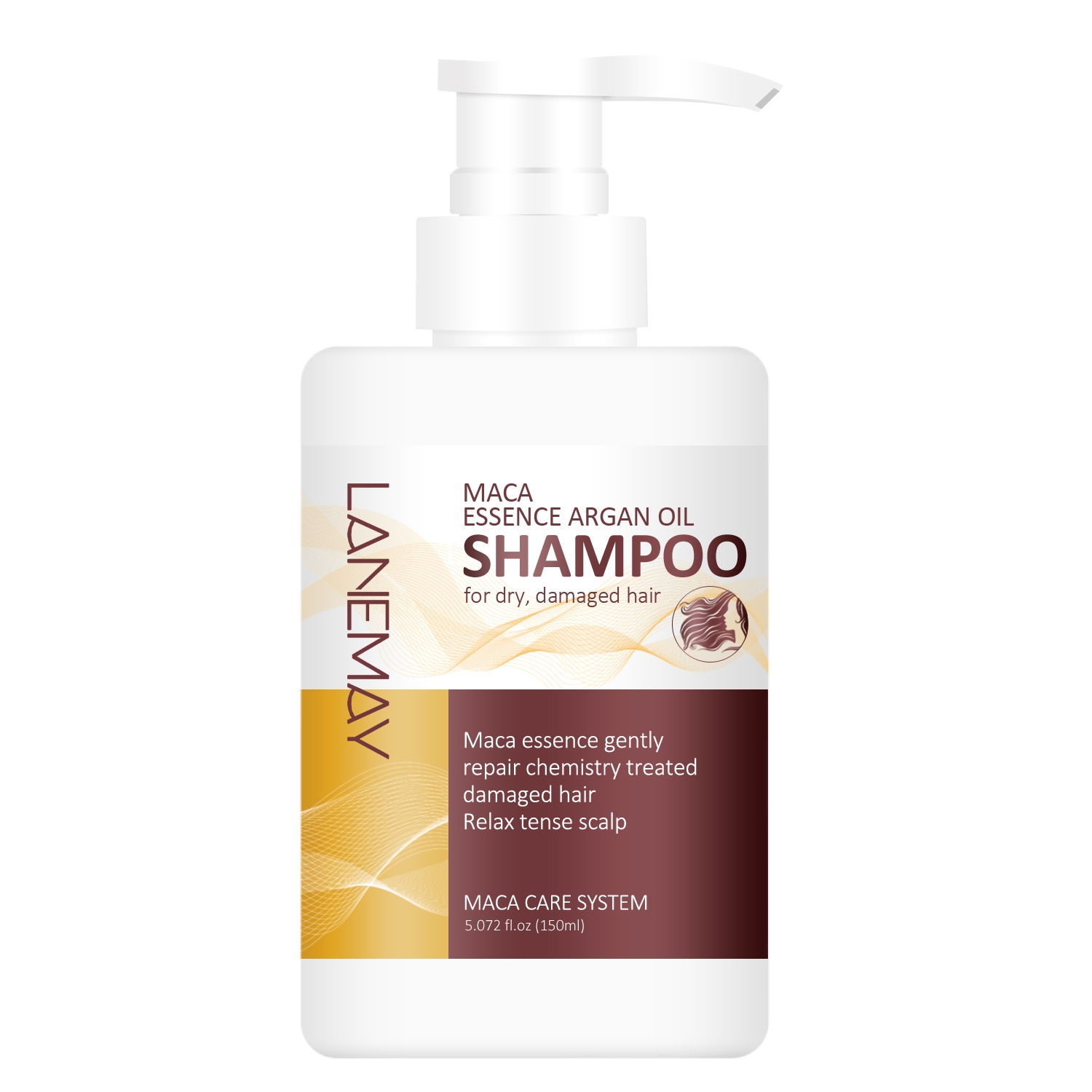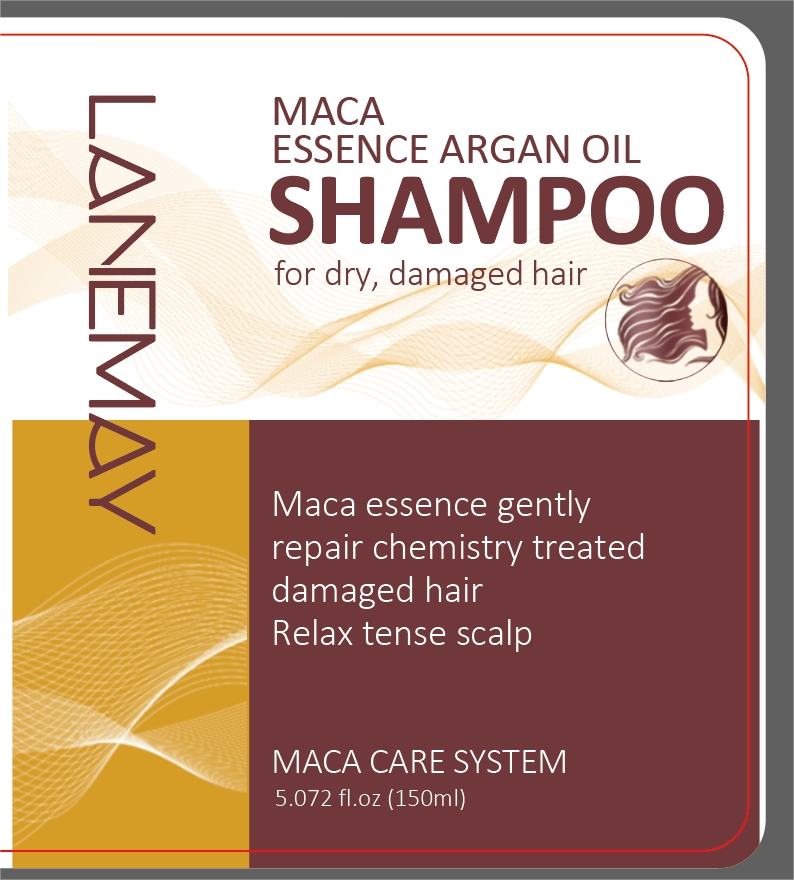 DRUG LABEL: Argan OilShampoo
NDC: 84025-068 | Form: EMULSION
Manufacturer: Guangzhou Yanxi Biotechnology Co., Ltd
Category: otc | Type: HUMAN OTC DRUG LABEL
Date: 20240716

ACTIVE INGREDIENTS: PHENOXYETHANOL 3 mg/150 mL; TREHALOSE 2 mg/150 mL
INACTIVE INGREDIENTS: WATER

DOSAGE AND ADMINISTRATION

Use as regular shampoo

WARNINGS

Keep out of Children

INACTIVE INGREDIENT

Aqua

INDICATIONS AND USAGE

Use as regular shampoo

Keep out of Children

PURPOSE

Promotes hair growth，Makes hair smoother